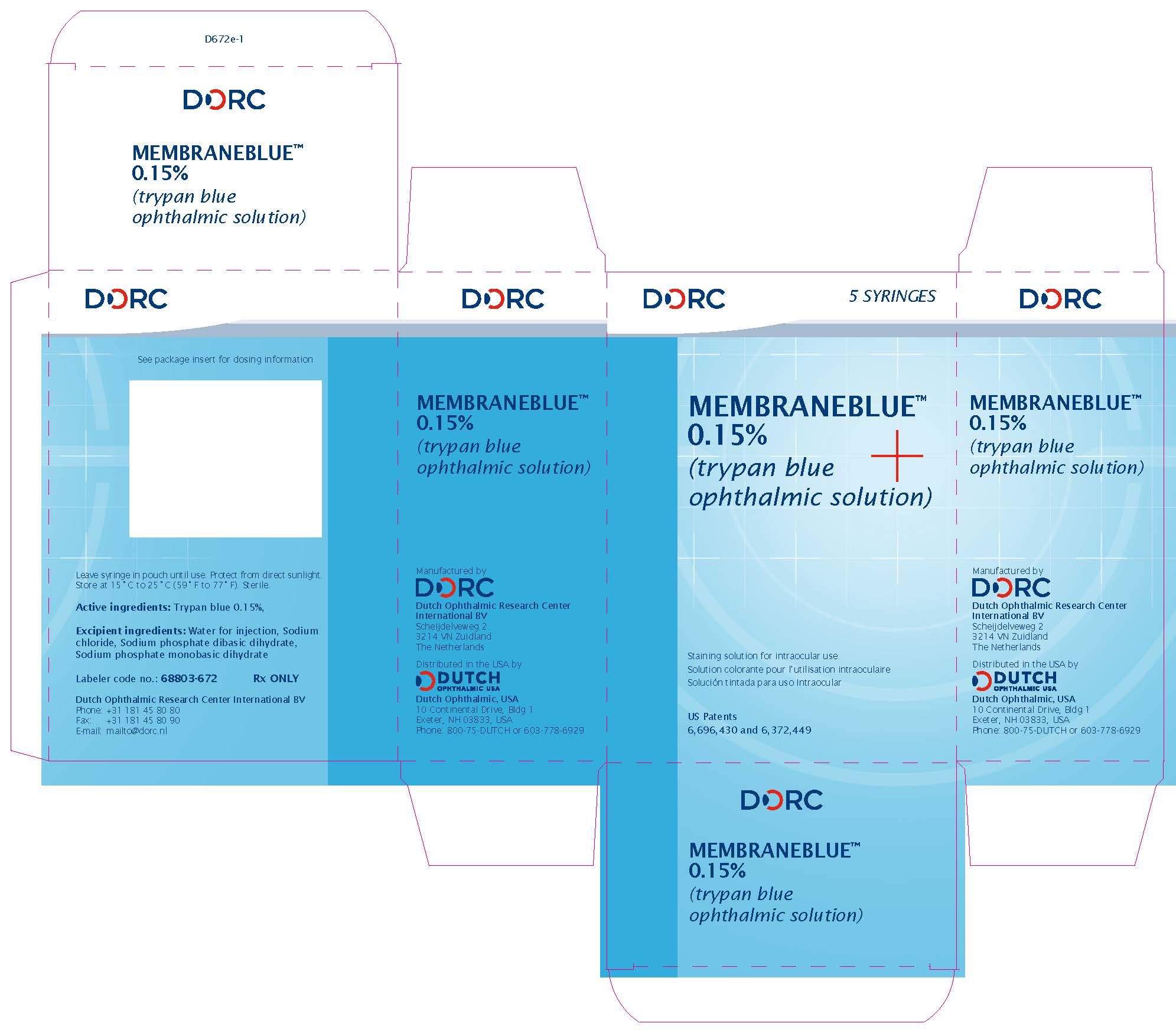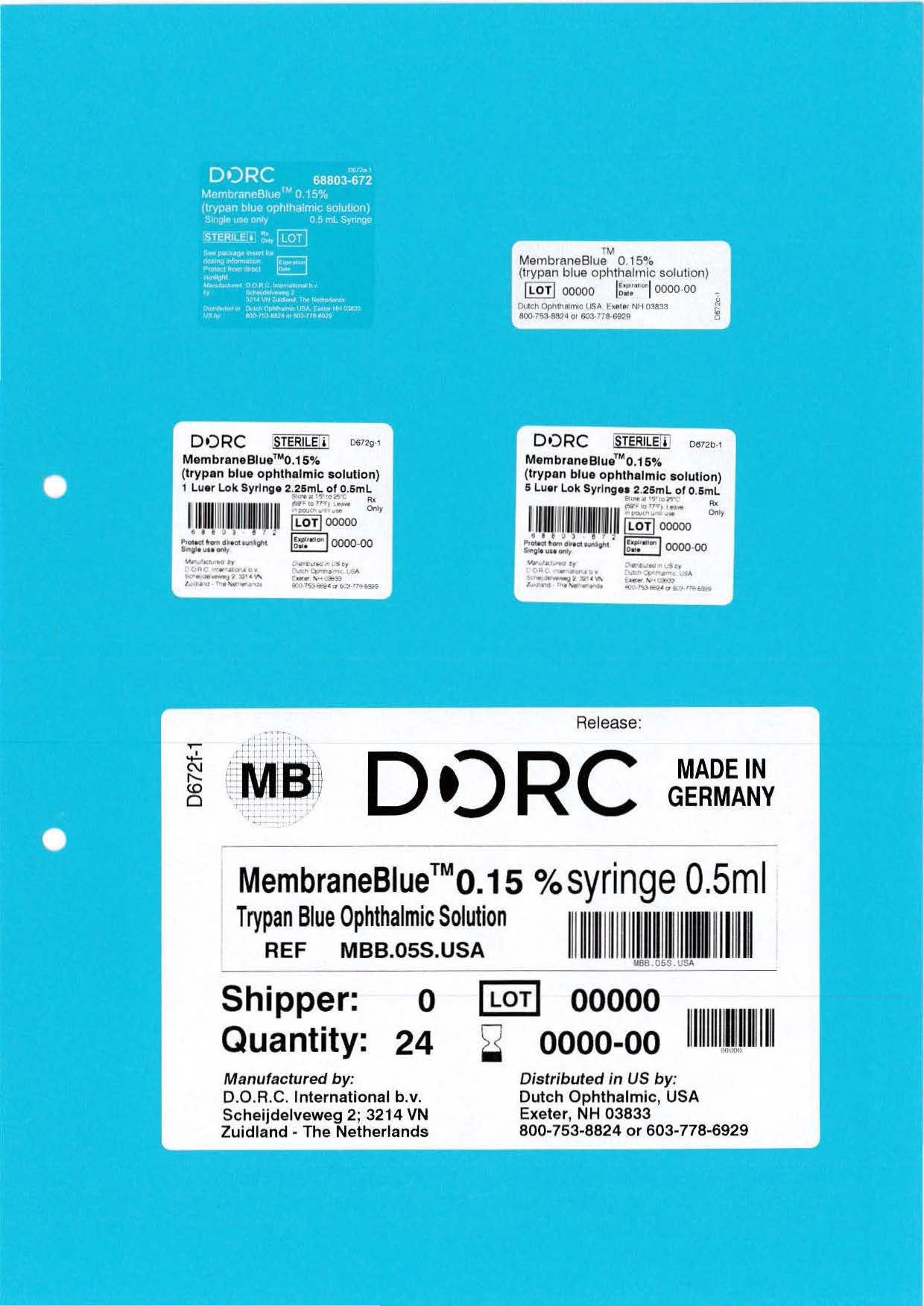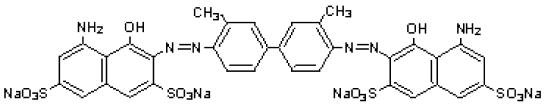 DRUG LABEL: MEMBRANEBLUE
NDC: 68803-672 | Form: INJECTION, SOLUTION
Manufacturer: Dutch Ophthalmic Research Center (International) B.V.
Category: prescription | Type: HUMAN PRESCRIPTION DRUG LABEL
Date: 20251124

ACTIVE INGREDIENTS: TRYPAN BLUE 0.75 mg/0.5 mL
INACTIVE INGREDIENTS: SODIUM PHOSPHATE, MONOBASIC, DIHYDRATE 0.15 mg/0.5 mL; WATER 0.5 mL/0.5 mL; SODIUM PHOSPHATE, DIBASIC, DIHYDRATE 0.95 mg/0.5 mL; SODIUM CHLORIDE 4.1 mg/0.5 mL

HIGHLIGHTS OF PRESCRIBING INFORMATION

MembraneBlue™ 0.15% (trypan blue ophthalmic solution). These highlights do not include all the information needed to use MembraneBlue™ 0.15% safely and effectively. See full prescribing information for MembraneBlue™ 0.15%. MembraneBlue™ 0.15% (trypan blue ophthalmic solution) Initial U.S. Approval: 2004

MembraneBlue 0.15% - Indications & Usage Section

These highlights do not include all the information needed to use MEMBRANEBLUE™ safely and effectively. See full prescribing information for MEMBRANEBLUE. MEMBRANEBLUE (trypan blue ophthalmic solution) 0.15%, for intraocular ophthalmic use Initial U.S. Approval: 2004

MembraneBlue is a diagnostic dye indicated for use as an aid in ophthalmic posterior surgery by staining the epiretinal membranes during ophthalmic surgical vitrectomy procedures, facilitating removal of epiretinal tissue in adults and pediatric patients

MembraneBlue 0.15% - Dosage & administration section

- Prior to injection of MembraneBlue, perform a “fluid-air exchange” (i.e., fill the entire vitreous cavity with air). Carefully apply MembraneBlue to epiretinal membranes using a blunt cannula and remove all excess dye.
  OR
- Inject MembraneBlue directly in a BSS filled-vitreous cavity. Wait 30 seconds and remove all excess dye. (2)

MembraneBlue 0.15% - Dosage forms & strengths section.

Ophthalmic solution: 0.15% trypan blue in a single-patient-use syringe.

MembraneBlue 0.15% - Contraindications section.

Insertion of a non-hydrated (dry state), hydrophilic acrylic intraocular lens (IOL). MembraneBlue may be absorbed by the IOL and stain it.

MembraneBlue 0.15% - Warnings and precautions section

- Excessive Staining: Excess MembraneBlue 0.15% should be immediately removed from the eye after staining.
- Priming of the Syringe: To make sure the plunger moves smoothly before use, first retract the plunger or twist the plunger in a clockwise motion before injecting the fluid.

MembraneBlue 0.15% - Adverse reactions section

Most common adverse reactions include discoloration of high water content hydrogen intraocular lenses and inadvertent staining of the posterior lens capsule and vitreous face.

To report SUSPECTED ADVERSE REACTIONS contact Dutch Ophthalmic, USA at 1-800-75-DUTCH or FDA at 1-800-FDA-1088 or www.fda.gov/medwatch.

MembraneBlue - Use in specific populations section

MembraneBlue should not be given to pregnant women

FULL PRESCRIBING INFORMATION

MembraneBlue 0.15% - Indications & Usage Section

MembraneBlue™ 0.15% is indicated for use as an aid in ophthalmic surgery by staining the epiretinal membranes during ophthalmic surgical vitrectomy procedures, facilitating removal of the tissue in adults and pediatric patients.

MembraneBlue 0.15% - Dosage & administration section

MembraneBlue 0.15% is packaged in a single-patient-use syringe filled to a volume of 0.5 mL. Make sure the plunger moves smoothly before use. Prime the syringe prior to use by retracting the plunger before injecting the fluid. Alternatively, twist the plunger into the stopper in a clockwise motion until tight. Once tight, continue turning the plunger in a clockwise motion until the stopper rotates freely within the syringe, two or three rotations. The syringe is now primed and suitable for injection.

Before injection of MembraneBlue perform a “fluid-air exchange” (i.e., filling the entire vitreous cavity with air, to prevent aqueous dilution of MembraneBlue). MembraneBlue is carefully applied to the retinal membrane using a blunt cannula attached to the MembraneBlue syringe, without allowing the cannula to contact or damage the retina. Sufficient staining is expected on contact with the membrane. All excess dye should be removed from the vitreous cavity before performing an air-fluid exchange, to prevent unnecessary spreading of the dye.

MembraneBlue can also be injected directly in a BSS filled vitreous cavity (instead of injecting under air). Clinical use demonstrated that, after complete vitreous and posterior hyaloid removal, sufficient staining is achieved after 30 seconds of application under BSS.

MembraneBlue is intended to be applied directly on the areas where membranes could be present, staining any portion of the membrane which comes in contact with the dye. The dye does not penetrate the membrane.

MembraneBlue 0.15% - Dosage forms & strengths section.

MembraneBlue (trypan blue ophthalmic solution) 0.15% is a clear, dark blue ophthalmic solution supplied in a 2.25 mL single-patient-use syringe filled to a volume of 0.5 mL.

MembraneBlue 0.15% - Contraindications section.

MembraneBlue 0.15% is contraindicated when a non-hydrated (dry state), hydrophilic acrylic intraocular lens (IOL) is planned to be inserted into the eye. The dye may be absorbed by the IOL and stain it.

MembraneBlue 0.15% - Warnings and precautions section

Excessive Staining

Excess MembraneBlue 0.15% should be immediately removed from the eye after staining.

Priming of the Syringe

To make sure the plunger moves smoothly before use, first retract the plunger or twist the plunger in a clockwise motion before injecting the fluid.

MembraneBlue 0.15% - Adverse reactions section

Adverse reactions reported following use of MembraneBlue 0.15% include discoloration of high water content hydrogen intraocular lenses [see Contraindications] and inadvertent staining of the posterior lens capsule and vitreous face. Staining of the posterior lens capsule or staining of the vitreous face is generally self limited, lasting up to one week.

MembraneBlue - Use in specific populations section

MembraneBlue - Pregnancy section

Risk Summary
There are no available data on the use of MembraneBlue 0.15% in pregnant women to inform a drug-associated risk of major birth defects, miscarriage, or adverse maternal or fetal outcomes. Systemic absorption of MembraneBlue 0.15% in humans is expected to be negligible following injection and subsequent removal of the drug at the completion of surgical procedures. Adequate animal reproduction studies were not conducted with MembraneBlue 0.15%, however, trypan blue has been shown to be teratogenic in various animal models at doses 323-fold and greater than the maximum recommended human dose, based on body surface area (BSA).

Due to the negligible human systemic exposure when used as recommended, it is not expected that maternal use of MembraneBlue will result in fetal exposure to the drug and risk of teratogenic effects.

Data

Animal Data

Trypan blue is teratogenic in rats, mice, rabbits, hamsters, dogs, guinea pigs, pigs, and chickens. The majority of teratogenicity studies performed involve intravenous, intraperitoneal, or subcutaneous administration in the rat. The teratogenic dose is 50 mg/kg as a single dose or 25 mg/kg/day during embryogenesis in the rat. Normalized to BSA, these doses are approximately 645- and 323-fold the maximum recommended human dose of 0.75 mg per injection (based on a 60 kg person), assuming complete systemic absorption of trypan blue. Characteristic anomalies included neural tube, cardiovascular, vertebral, tail, and eye defects. Trypan blue also caused an increase in post-implantation mortality and decreased fetal weight. In the monkey, trypan blue caused abortions with single or two daily doses of 50 mg/kg between 20th to 25th days of pregnancy, but no apparent increase in birth defects (approximately 1,300-fold the maximum recommended human dose based on BSA, assuming complete systemic absorption).

MembraneBlue - Lactation section

Risk Summary

The presence of trypan blue in human milk following intraocular administration of trypan blue has not been evaluated. There are no data available regarding the effects of trypan blue on milk production. Breastfeeding is not expected to result in exposure of the child to trypan blue due to
the negligible systemic exposure of trypan blue in humans following injection and subsequent removal of the drug at the completion of surgical procedures.

MembraneBlue - Pediatric use section

The safety and effectiveness of trypan blue have been established in pediatric patients. Use of trypan blue is supported by evidence from an adequate and well-controlled study in pediatric patients.

MembraneBlue - Geriatric use

No overall differences in safety and effectiveness were observed between elderly and younger patients.

MembraneBlue - Description.

MembraneBlue™ (trypan blue ophthalmic solution) 0.15% is a sterile solution of trypan blue (an acid di-azo group dye) for intraocular ophthalmic use. MembraneBlue selectively stains epiretinal membranes during ophthalmic surgical vitrectomy procedures.

Each mL of MembraneBlue 0.15% contains: 1.5 mg trypan blue; 1.9 mg sodium mono-hydrogen orthophosphate (Na2HPO4•2H2O); 0.3 mg sodium di-hydrogen orthophosphate (NaH2PO4•2H2O); 8.2 mg sodium chloride (NaCl); and water for injection. The pH is 7.3 - 7.6. The osmolality is 257 - 314 mOsm/kg.

The drug substance trypan blue has the chemical name 3,3'-[(3,3'-dimethyl-4,4'-biphenylylene) bis (azo)] bis (5-amino-4-hydroxy-2,7-naphthalenedisulfonic acid) tetra sodium salt, a molecular weight of 960.8, a molecular formula of C34H24N6Na4O14S4, and has the following chemical structure:

MembraneBlue - Clinical Pharmacology Section

MembraneBlue 0.15% - Mechanism of action section.

MembraneBlue 0.15% selectively stains membranes in the human eye during posterior surgery, such as epiretinal membranes (ERM) and Internal Limiting Membranes (ILM).

MembraneBlue - Nonclinical toxicology section

Carinogenesis, Mutagenesis, Impairment of Fertility

Carcinogenesis

Trypan blue is carcinogenic in rats. Wister/Lewis rats developed lymphomas after receiving subcutaneous injections of 1% trypan blue dosed at 50 mg/kg every other week for 52 weeks (approximately 645-fold the maximum recommended human dose of 0.75 mg per injection in a 60 kg person based on BSA, assuming complete systemic absorption).

Mutagenesis
Trypan blue was mutagenic in the Ames test and caused DNA strand breaks in vitro.

MembraneBlue - How supplied section

MembraneBlue (trypan blue ophthalmic solution) 0.15% is a clear, dark blue ophthalmic solution supplied as follows:

0.5 mL of MembraneBlue 0.15% in a sterile single-patient-use Luer Lock, 2.25 mL glass syringe, grey rubber plunger stopper and tip cap with polypropylene plunger rod in a peel pouch. Five pouched products are packed in one distribution box.

NDC 68803-672-01 (One 0.5 mL syringe)
NDC 68803-672-05 (Carton of five 0.5 mL syringes)

MembraneBlue - Storage and handling section

Storage: Store between 15ºC to 25ºC (59ºF to 77ºF). Protect from direct sunlight. Single-patient-use. Discard unused portion.

Made in Germany

Distributed in the United States by

Dutch Ophthalmic, USA

10, Continental Drive, Bldg 1

Exeter, NH 03833, USA

Phone: 800-75-DUTCH or 603-778-6929